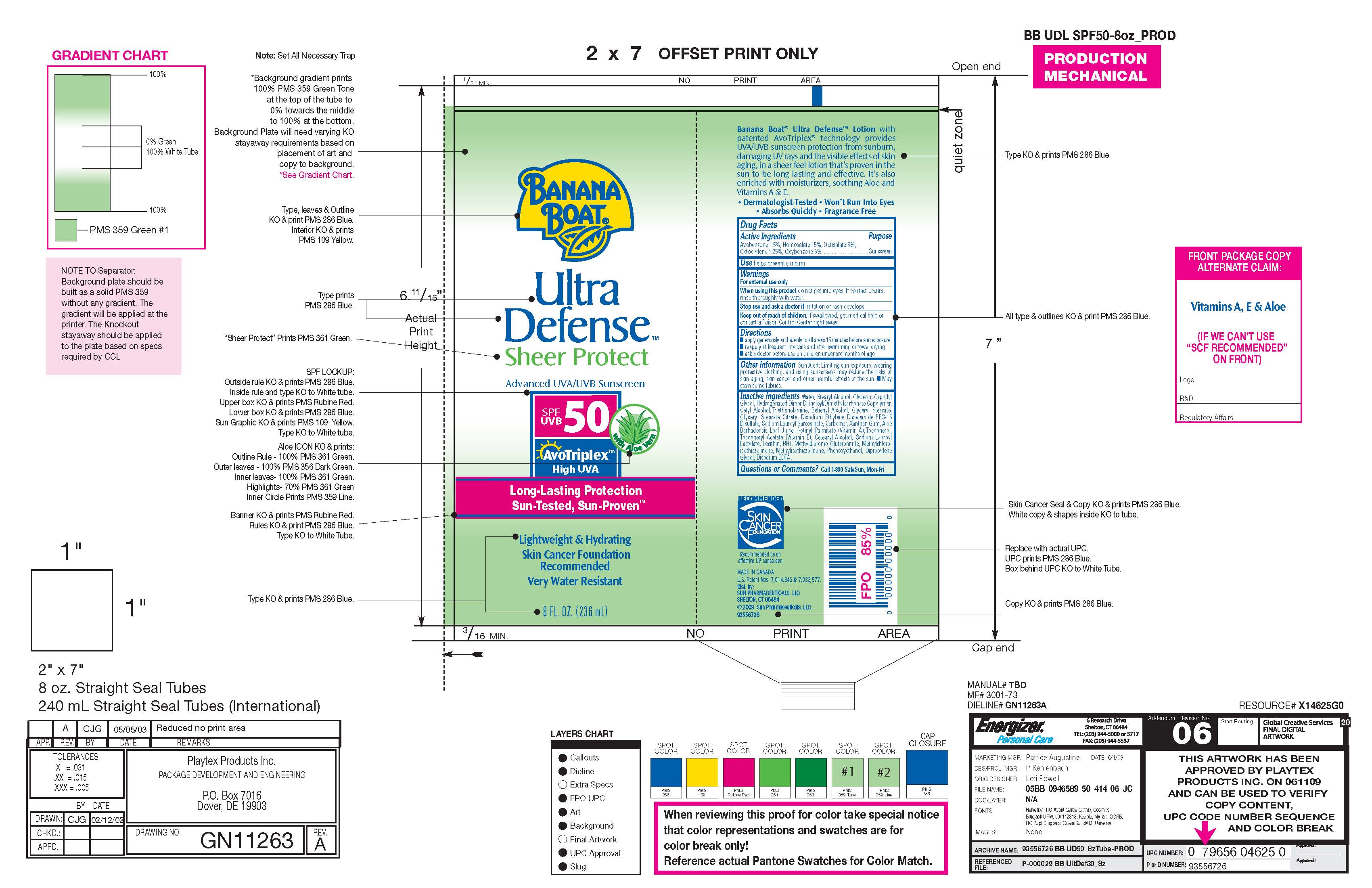 DRUG LABEL: Banana Boat Ultra Defense
NDC: 61047-819 | Form: LOTION
Manufacturer: KIK Custom Products
Category: otc | Type: HUMAN OTC DRUG LABEL
Date: 20100325

ACTIVE INGREDIENTS: Avobenzone 3.54 mL/236 mL; Homosalate 35.4 mL/236 mL; Octisalate 11.8 mL/236 mL; Octocrylene 2.95 mL/236 mL; Oxybenzone 14.16 mL/236 mL

Banana Boat Ultra Defense Sheer Protect Advanced UVA/UVB Sunscreen SPF UVB50 -Long Lasting Protection, Sun Tested, Sun Proven

Drug Facts:
Avobenzone: 1.5%
Homosalate: 15%
Octisalate: 5%
Octicrylene: 1.25%
Oxybenzone: 6%
Purpose: Sunscreen

WARNINGS

FOR EXTERNAL USE ONLY.
WHEN USING THIS PRODUCT, DO NOT GET INTO EYES IF CONTACT OCCURS, RINSE THOROUGHLY WITH WATER.
STOP USE AND ASK DOCTOR IF IRRITATION OR RASH DEVELOPS. KEEP OUT OF REACH OF CHILDREN.
IF SWALLOWED, GET MEDICAL HELP OR CONTACT POISON CONTROL CENTER RIGHT AWAY.

INACTIVE INGREDIENT

Water, Cetearyl Alcohol, Glycerin, Capryly Glycol, Hydrogenated Dimer Dilnoleyl/Dimethyl Carbonate,
Copolymer, Cetyl Alcohol, Triethanolamine, Behenyl Acohol, Glyceryl Stearate, Glyceryl Stearate, Citrate,
Disodium Ethylene, Dicocamide PEG-15 Disulfate, Sodium Lauroyl Sarcosinate, Carbomer, Xanthan Gum,
Aloe Barbadensis Leaf Juice, Retinyl Palmitate (Vitamin A), Tocopherol, Tocopheryl Acetate (Vitamin E),
Cetearyl Alchol, Sodium Lauroyl, Lactylate, Lecithin, BHT, Methyl Dibromo Glutaronitrile, Methyl Chloisothiazolinone.
Methyl Isothiazolinone, Phenoxy Ethanol, Dipropylene Glycol, Disodium EDTA

Questions or Comments: Call 1-800-SAFESUN Mon-Fri.